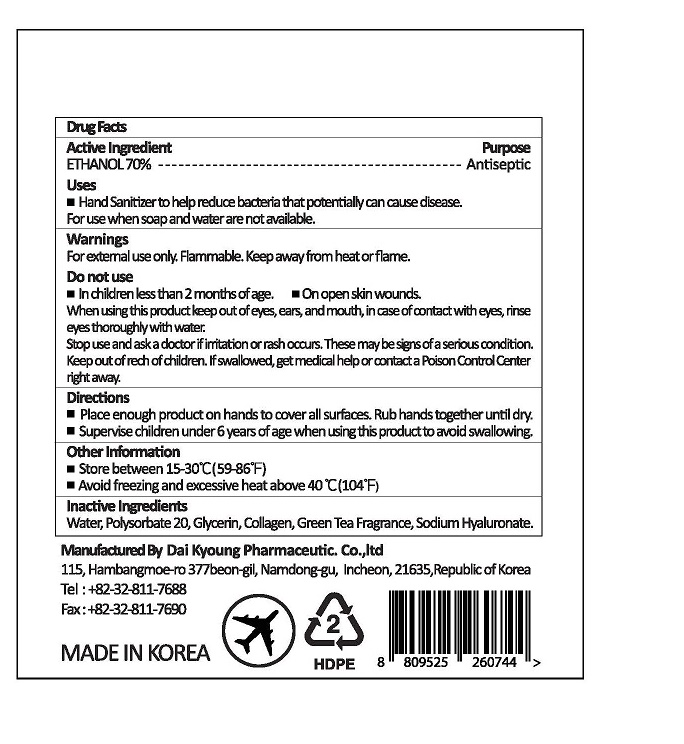 DRUG LABEL: Nature Hand Touch Sanitizer Liquid (ethanol) 70%
NDC: 74279-0020 | Form: LIQUID
Manufacturer: Dai Kyoung Pharmaceutic Co.,Ltd.
Category: otc | Type: HUMAN OTC DRUG LABEL
Date: 20210829

ACTIVE INGREDIENTS: ALCOHOL 70 mL/100 mL
INACTIVE INGREDIENTS: WATER; POLYSORBATE 20; GLYCERIN; HYALURONATE SODIUM

PLUS / Dai Kyoung Pharmaceutic Co.,Ltd.

ACTIVE INGREDIENT

Alcohol (Ethanol)

INACTIVE INGREDIENT

Polysorbate 20, Gylcerin, cherry Fragrance, Sodium Hyaluronate, Collagen, Water

PURPOSE

Hand sanitizer to help reduce bacteria that potentially can cause disease. For use when soap and water are not available.

keep out of reach of the children

INDICATIONS AND USAGE

Place enough product on hands to cover all surfaces. Rub hands together until dry.

Supervise children under 6 years of age when using this product to avoid swallowing.

WARNINGS

For external use only. Flammable. Keep away from heat or flame.

Do not use

- in children less than 2 months of age
- on open skin wounds

When using this product keep out of eyes, ears, and mouth. In case of contact with eyes, rinse thoroughly with water.

Stop use and ask a doctor if irritation or rash occurs. These may be signs of a serious condition.

Keep out of reach of children. If swallowed, get medical help or contact a Poison Control Center right away.

DOSAGE AND ADMINISTRATION

for external use only